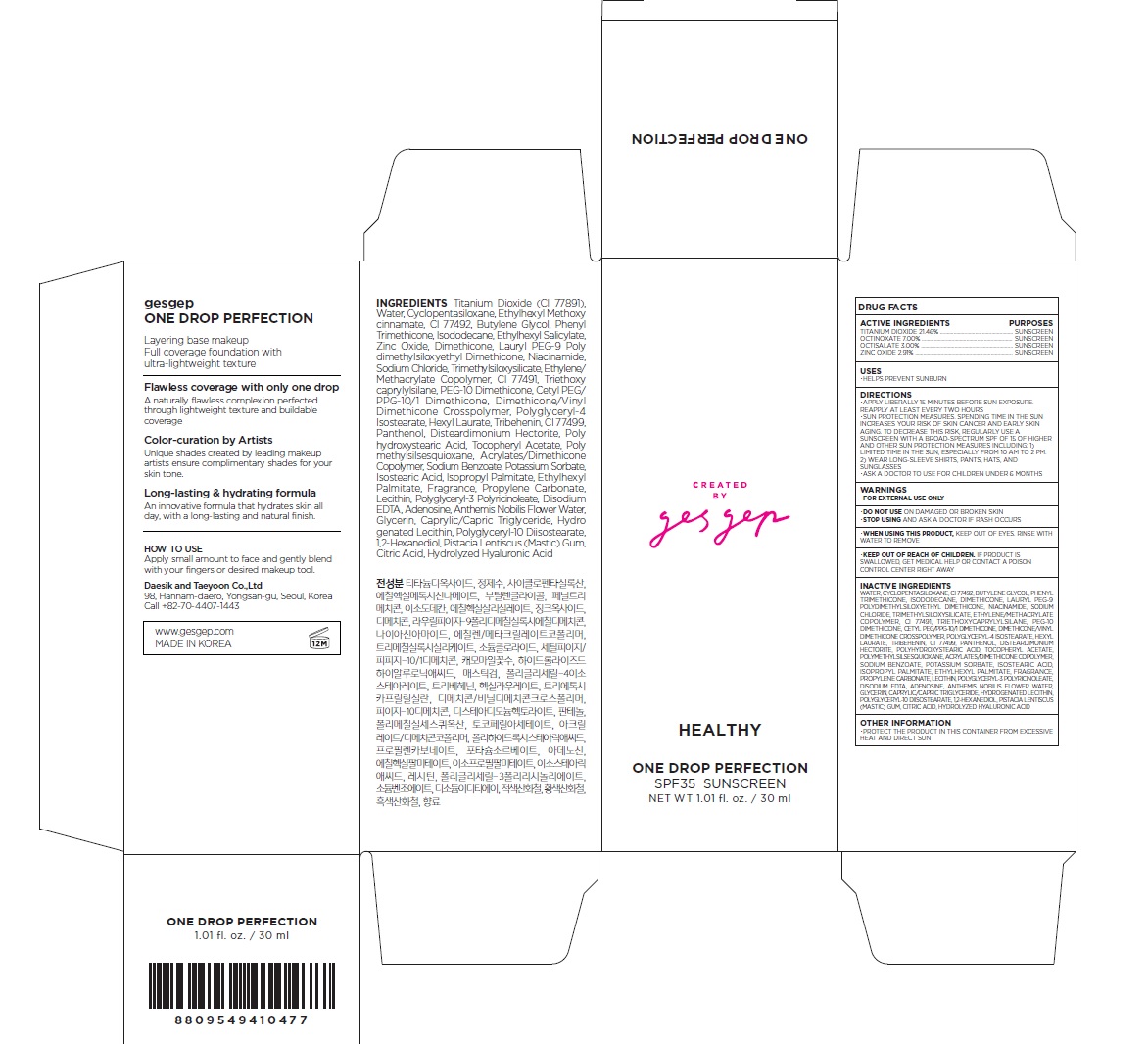 DRUG LABEL: gesgep ONE DROP PERFECTION HEALTHY
NDC: 71407-003 | Form: CREAM
Manufacturer: Daesik and Taeyoon Co., Ltd.
Category: otc | Type: HUMAN OTC DRUG LABEL
Date: 20170515

ACTIVE INGREDIENTS: TITANIUM DIOXIDE 6.438 mg/30 mL; OCTINOXATE 2.1 mg/30 mL; OCTISALATE 0.9 mg/30 mL; ZINC OXIDE 0.873 mg/30 mL
INACTIVE INGREDIENTS: Water; CYCLOMETHICONE 5; BUTYLENE GLYCOL; Phenyl Trimethicone; Isododecane; Dimethicone; Niacinamide; LAURYL PEG-9 POLYDIMETHYLSILOXYETHYL DIMETHICONE; TRIMETHYLSILOXYSILICATE (M/Q 0.6-0.8); SODIUM CHLORIDE; FERRIC OXIDE YELLOW; PEG-10 DIMETHICONE (600 CST); CETYL PEG/PPG-10/1 DIMETHICONE (HLB 2); TRIETHOXYCAPRYLYLSILANE; Polyglyceryl-4 Isostearate; Hexyl Laurate; Tribehenin; Panthenol; Disteardimonium Hectorite; POLYHYDROXYSTEARIC ACID (2300 MW); .ALPHA.-TOCOPHEROL ACETATE; POLYMETHYLSILSESQUIOXANE (4.5 MICRONS); FERRIC OXIDE RED; SODIUM BENZOATE; Potassium Sorbate; Isostearic Acid; Propylene Carbonate; Isopropyl Palmitate; Ethylhexyl Palmitate; FERROSOFERRIC OXIDE; EDETATE DISODIUM ANHYDROUS; ADENOSINE; CHAMAEMELUM NOBILE FLOWER OIL; GLYCERIN; MEDIUM-CHAIN TRIGLYCERIDES; HYDROGENATED SOYBEAN LECITHIN; 1,2-Hexanediol; PISTACIA LENTISCUS RESIN; CITRIC ACID MONOHYDRATE

Drug Facts

ACTIVE INGREDIENT

Titanium Dioxide 21.49%

Octinoxate 7.00%

Octisalate 3.00%

Zinc Oxide 2.91%

PURPOSE

Sunscreen

INDICATIONS AND USAGE

Helps prevent sunburn

DOSAGE AND ADMINISTRATION

Apply liberally 15 minutes before sun exposure.

Reapply at least every two hours

Sun protection measures. Spending time in the sun increases your risk of skin cancer and early skin aging. To decrease this risk, regularly use a sunscreen with a broad spectrum SPF of 15 of higher and other sun protection measures including: 1) Limited time in the sun, especially from 10 am to 2 pm. 2) Wear long-sleeve shirts, pants, hats, and sunglasses
Ask a doctor to use for children under 6 months

WARNINGS

For external use only.
Do not use on damaged or broken skin.
When using this product, keep out of eyes. Rinse with water to remove.
Stop using and ask a doctor if rash occurs.

KEEP OUT OF REACH OF CHILDREN

Keep out of reach of the children. If product is swallowed, get medical help or contact a poison control center right away.

INACTIVE INGREDIENT

Water
Cyclopentasiloxane
Butylene Glycol
Phenyl Trimethicone
Isododecane
Dimethicone
Niacinamide
Lauryl PEG-9 Polydimethylsiloxyethyl Dimethicone
Trimethylsiloxysilicate
Sodium Chloride
Ethylene/Methacrylate Copolymer
CI 77492
PEG-10 Dimethicone
Cetyl PEG/PPG-10/1 Dimethicone
Dimethicone/Vinyl Dimethicone Crosspolymer
Triethoxycaprylylsilane
Polyglyceryl-4 Isostearate
Hexyl Laurate
Tribehenin
Panthenol
Disteardimonium Hectorite
Polyhydroxystearic Acid
Tocopheryl Acetate
Polymethylsilsesquioxane
CI 77491
Acrylates/Dimethicone Copolymer
Sodium Benzoate
Potassium Sorbate
Isostearic Acid
Lecithin
Fragrance
Propylene Carbonate
Isopropyl Palmitate
Ethylhexyl Palmitate
CI 77499
Polyglyceryl-3 Polyricinoleate
Disodium EDTA
Adenosine
Anthemis Nobilis Flower Water
Glycerin
Caprylic/Capric Triglyceride
Polyglyceryl-10 Diisostearate
Hydrogenated Lecithin
1,2-Hexanediol
Pistacia Lentiscus (Mastic) Gum
Citric Acid
Hydrolyzed Hyaluronic Acid